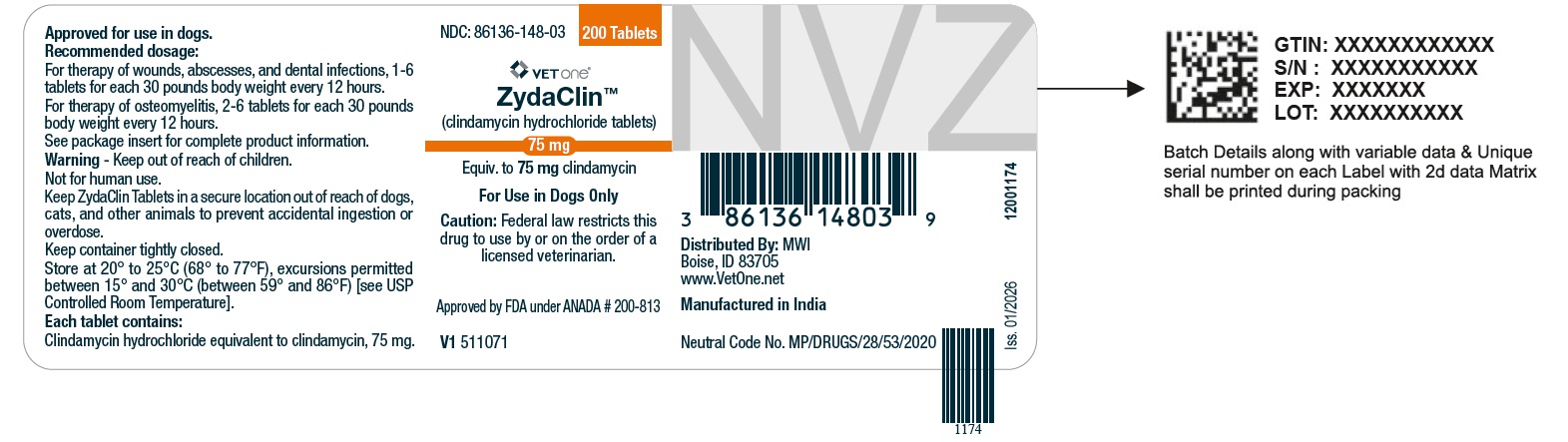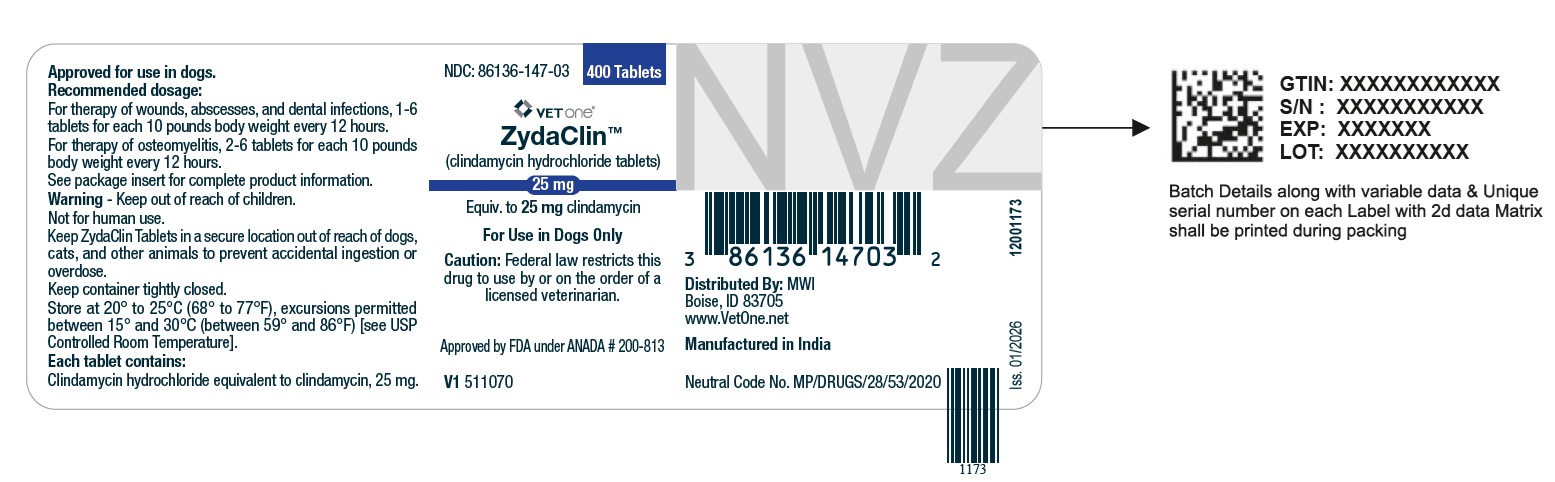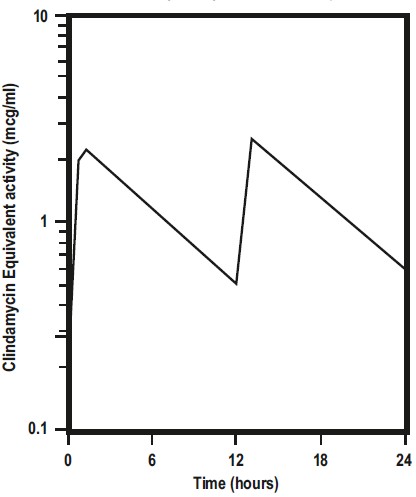 DRUG LABEL: Clindamycin Hydrochloride
NDC: 86136-147 | Form: TABLET
Manufacturer: MWI/Vetone
Category: animal | Type: Prescription Animal Drug Label
Date: 20260218

ACTIVE INGREDIENTS: CLINDAMYCIN HYDROCHLORIDE 25 mg/1 1

ZydaClin
(clindamycin hydrochloride tablets)

Caution

Federal law restricts this drug to use by or on the order of a licensed veterinarian.

DESCRIPTION

ZydaClinTM contain clindamycin hydrochloride which is the hydrated salt of clindamycin. Clindamycin is a semisynthetic antibiotic produced by a 7(S)- chlorosubstitution of the 7(R)-hydroxyl group of a naturally produced antibiotic produced by Streptomyces lincolnensis var. lincolnensis.

ZydaClin Tablets (For Use in Dogs Only):

25 mg Tablet, each white to off white colored round shaped tablet contains clindamycin hydrochloride equivalent to 25 mg of clindamycin.

75 mg Tablet, each white to off white colored round shaped tablet contains clindamycin hydrochloride equivalent to 75 mg of clindamycin.

150 mg Tablet, each white to off white colored round shaped tablet, contains clindamycin hydrochloride equivalent to 150 mg of clindamycin.

CLINICAL PHARMACOLOGY

Absorption

Clindamycin hydrochloride is rapidly absorbed from the canine gastrointestinal tract.

Dog Serum Levels

Serum levels at or above 0.5 μg/mL can be maintained by oral dosing at a rate of 2.5 mg/lb of clindamycin hydrochloride every 12 hours. This same study revealed that average peak serum concentrations of clindamycin occur 1 hour and 15 minutes after oral dosing. The elimination half-life for clindamycin in dog serum was approximately 5 hours. There was no bioactivity accumulation after a regimen of multiple oral doses in healthy dogs.

Clindamycin Serum Concentrations 2.5 mg/lb (5.5 mg/kg) After B.I.D. Oral Dose of Clindamycin Hydrochloride Capsules to Dogs

Metabolism and Excretion

Extensive studies of the metabolism and excretion of clindamycin hydrochloride administered orally in animals and humans have shown that unchanged drug and bioactive and bioinactive metabolites are excreted in urine and feces. Almost all of the bioactivity detected in serum after clindamycin hydrochloride product administration is due to the parent molecule (clindamycin). Urine bioactivity, however, reflects a mixture of clindamycin and active metabolites, especially N-demethyl clindamycin and clindamycin sulfoxide.

Site and Mode of Action

Clindamycin is an inhibitor of protein synthesis in the bacterial cell. The site of binding appears to be in the 50S sub-unit of the ribosome. Binding occurs to the soluble RNA fraction of certain ribosomes, thereby inhibiting the binding of amino acids to those ribosomes. Clindamycin differs from cell wall inhibitors in that it causes irreversible modification of the protein-synthesizing subcellular elements at the ribosomal level.

Microbiology

Clindamycin is a lincosaminide antimicrobial agent with activity against a wide variety of aerobic and anaerobic bacterial pathogens. Clindamycin is a bacteriostatic compound that inhibits bacterial protein synthesis by binding to the 50S ribosomal sub-unit. The minimum inhibitory concentrations (MICs) of Gram-positive and obligate anaerobic pathogens isolated from dogs in the United States are presented in Table 1. Bacteria were isolated in 1998-1999. All MICs were performed in accordance with the Clinical and Laboratory Standards Institute (CLSI).

Table 1. Clindamycin MIC Values (μg/mL) from Diagnostic Laboratory Survey Data Evaluating Canine Pathogens in the U.S. during 1998-99^1

Organism | Number of Isolates | MIC50 | MIC85 | MIC90 | Range
Soft Tissue/Wound^2
Staphylococcus aureus | 17 | 0.5 | 0.5 | ≥ 4.0 | 0.25 - ≥ 4.0
Staphylococcus intermedius | 28 | 0.25 | 0.5 | ≥ 4.0 | 0.125 - ≥ 4.0
Staphylococcus spp. | 18 | 0.5 | 0.5 | ≥ 4.0 | 0.25 - ≥ 4.0
Beta-hemolytic streptococci | 46 | 0.5 | 0.5 | ≥ 4.0 | 0.25 - ≥ 4.0
Streptococcus spp. | 11 | 0.5 | ≥ 4.0 | ≥ 4.0 | 0.25 - ≥ 4.0
Osteomyelitis/Bone^3
Staphylococcus aureus | 20 | 0.5 | 0.5 | 0.5 | 0.5^4
Staphylococcus intermedius | 15 | 0.5 | ≥ 4.0 | ≥ 4.0 | 0.25 - ≥ 4.0
Staphylococcus spp. | 18 | 0.5 | ≥ 4.0 | ≥ 4.0 | 0.25 - ≥ 4.0
Beta-hemolytic streptococci | 21 | 0.5 | 2.0 | 2.0 | 0.25 - ≥ 4.0
Streptococcus spp. | 21 | ≥ 4.0 | ≥ 4.0 | ≥ 4.0 | 0.25 - ≥ 4.0
Dermal/Skin^5
Staphylococcus aureus | 25 | 0.5 | ≥ 4.0 | ≥ 4.0 | 0.25 - ≥ 4.0
Staphylococcus intermedius | 48 | 0.5 | ≥ 4.0 | ≥ 4.0 | 0.125 - ≥ 4.0
Staphylococcus spp. | 32 | 0.5 | ≥ 4.0 | ≥ 4.0 | 0.25 - ≥ 4.0
Beta-hemolytic streptococci | 17 | 0.5 | 0.5 | 0.5 | 0.25 - 0.5

^1The correlation between the in vitro susceptibility data and clinical response has not been determined.

^2Soft Tissue/Wound: includes samples labeled wound, abscess, aspirate, exudates, draining tract, lesion, and mass

^3Osteomyelitis/Bone: includes samples labeled bone, fracture, joint, tendon

^4No range, all isolates yielded the same value

^5Dermal/Skin: includes samples labeled skin, skin swab, biopsy, incision, lip

INDICATIONS

ZydaClinTM Tablets (for use in dogs only) are indicated for the treatment of infections caused by susceptible strains of the designated microorganisms in the specific conditions listed below:

Dogs : Skin infections (wounds and abscesses) due to coagulase positive staphylococci (Staphylococcus aureus or Staphylococcus intermedius). Deep wounds and abscesses due to Bacteroides fragilis, Prevotella melaninogenicus, Fusobacterium necrophorum and Clostridium perfringens. Dental infections due to Staphyloccus aureus, Bacteroides fragilis, Prevotella melaninogenicus, Fusobacterium necrophorum and Clostridium perfringens. Osteomyelitis due to Staphylococcus aureus, Bacteroides fragilis, Prevotella melaninogenicus, Fusobacterium necrophorum and Clostridium perfringens.

CONTRAINDICATIONS

ZydaClin Tablets are contraindicated in animals with a history of hypersensitivity to preparations containing clindamycin or lincomycin.
Because of potential adverse gastrointestinal effects, do not administer to rabbits, hamsters, guinea pigs, horses, chinchillas or ruminating animals.

WARNINGS

Keep out of reach of children. Not for human use.

Keep ZydaClin Tablets in a secure location out of reach of dogs, cats, and other animals to prevent accidental ingestion or overdose.

PRECAUTIONS

During prolonged therapy of one month or greater, periodic liver and kidney function tests and blood counts should be performed.

The use of clindamycin hydrochloride occasionally results in overgrowth of non-susceptible organisms such as clostridia and yeasts. Therefore, the administration of ZydaClin Tablets should be avoided in those species sensitive to the gastrointestinal effects of clindamycin (see CONTRAINDICATIONS). Should superinfections occur, appropriate measures should be taken as indicated by the clinical situation.

Patients with very severe renal disease and/or very severe hepatic disease accompanied by severe metabolic aberrations should be dosed with caution, and serum clindamycin levels monitored during high-dose therapy.

Clindamycin hydrochloride has been shown to have neuromuscular blocking properties that may enhance the action of other neuromuscular blocking agents. Therefore, ZydaClin Tablets should be used with caution in animals receiving such agents.

Safety in gestating bitches or breeding male dogs has not been established.

ADVERSE REACTIONS

Side effects occasionally observed in either clinical trials or during clinical use were vomiting and diarrhea.

CONTACT INFORMATION

To report suspected adverse drug experiences, for technical assistance or to obtain a copy of the Safety Data Sheet, contact Felix Pharmaceuticals Private Limited at 1-833-571-1525. For additional information about adverse drug experience reporting for animal drugs, contact FDA at 1-888-FDA-VETS or http://www.fda.gov/reportanimalae

DOSAGE AND ADMINISTRATION

Dogs: Infected Wounds, Abscesses, and Dental Infections

Oral: 2.5-15.0 mg/lb body weight every 12 hours

Duration: Treatment with ZydaClin Tablets may be continued up to a maximum of 28 days if clinical judgment indicates. Treatment of acute infections should not be continued for more than three or four days if no response to therapy is seen.

Dosage Schedule

Tablets
ZydaClin Tablets 25 mg, administer 1-6 tablets every 12 hours for each 10 pounds of body weight.

ZydaClin Tablets 75 mg, administer 1-6 tablets every 12 hours for each 30 pounds of body weight.

ZydaClin Tablets 150 mg, administer 1-6 tablets every 12 hours for each 60 pounds of body weight.

Dogs: Osteomyelitis

Oral: 5.0-15.0 mg/lb body weight every 12 hours

Duration: Treatment with ZydaClin Tablets is recommended for a minimum of 28 days. Treatment should not be continued for longer than 28 days if no response to therapy is seen.

Dosage Schedule

Tablets
ZydaClin Tablets 25 mg, administer 2-6 tablets every 12 hours for each 10 pounds of body weight.
ZydaClin Tablets 75 mg, administer 2-6 tablets every 12 hours for each 30 pounds of body weight.
ZydaClin Tablets 150 mg, administer 2-6 tablets every 12 hours for each 60 pounds of body weight.

ANIMAL SAFETY SUMMARY

Rat and Dog Data: One year oral toxicity studies in rats and dogs at doses of 30, 100 and 300 mg/kg/day (13.6, 45.5 and 136.4 mg/lb/day) have shown clindamycin hydrochloride capsules to be well tolerated. Differences did not occur in the parameters evaluated to assess toxicity when comparing groups of treated animals with contemporary controls. Rats administered clindamycin hydrochloride at 600 mg/kg/day (272.7 mg/lb/day) for six months tolerated the drug well; however, dogs orally dosed at 600 mg/kg/day (272.7 mg/lb/day) vomited, had anorexia, and subsequently lost weight. At necropsy these dogs had erosive gastritis and focal areas of necrosis of the mucosa of the gallbladder.

Safety in gestating bitches or breeding males has not been established.

STORAGE

Store at 20° to 25°C (68° to 77°F), excursions permitted between 15° and 30°C (between 59° and 86°F) [see USP Controlled Room Temperature].

HOW SUPPLIED

ZydaClinTM Tablets are available as:

- 25 mg - bottles of 400
- 75 mg - bottles of 200
- 150 mg - bottles of 100

NDC Number | Tablet Size | Tablets/Bottle
86101-147-03 | 25 mg | 400
86101-148-03 | 75 mg | 200
XXXX-XXX-XX | 150 mg | 100

Approved by FDA under ANADA # 200-813

Distributed By:

MWI
Boise, ID 83705
www.VetOne.net

Manufactured in India

Neutral Code No. MP/DRUGS/28/53/2020

Rev. 01/2026

PACKAGE LABEL.PRINCIPAL DISPLAY PANEL

NDC: 86136-147-03 400 Tablets

ZydaClinTM (Clindamycin Hydrochloride Tablets)

25 mg

Equiv. to 25 mg clindamycin

For Use in Dogs Only

Caution: Federal law restricts this drug to use by or on the order of a licensed veterinarian.

Approved by FDA under ANADA # 200-813

PACKAGE LABEL.PRINCIPAL DISPLAY PANEL

NDC: 86136-148-03 200 Tablets

ZydaClinTM (Clindamycin Hydrochloride Tablets)

75 mg

Equiv. to 75 mg clindamycin

For Use in Dogs Only

Caution: Federal law restricts this drug to use by or on the order of a licensed veterinarian.

Approved by FDA under ANADA # 200-813